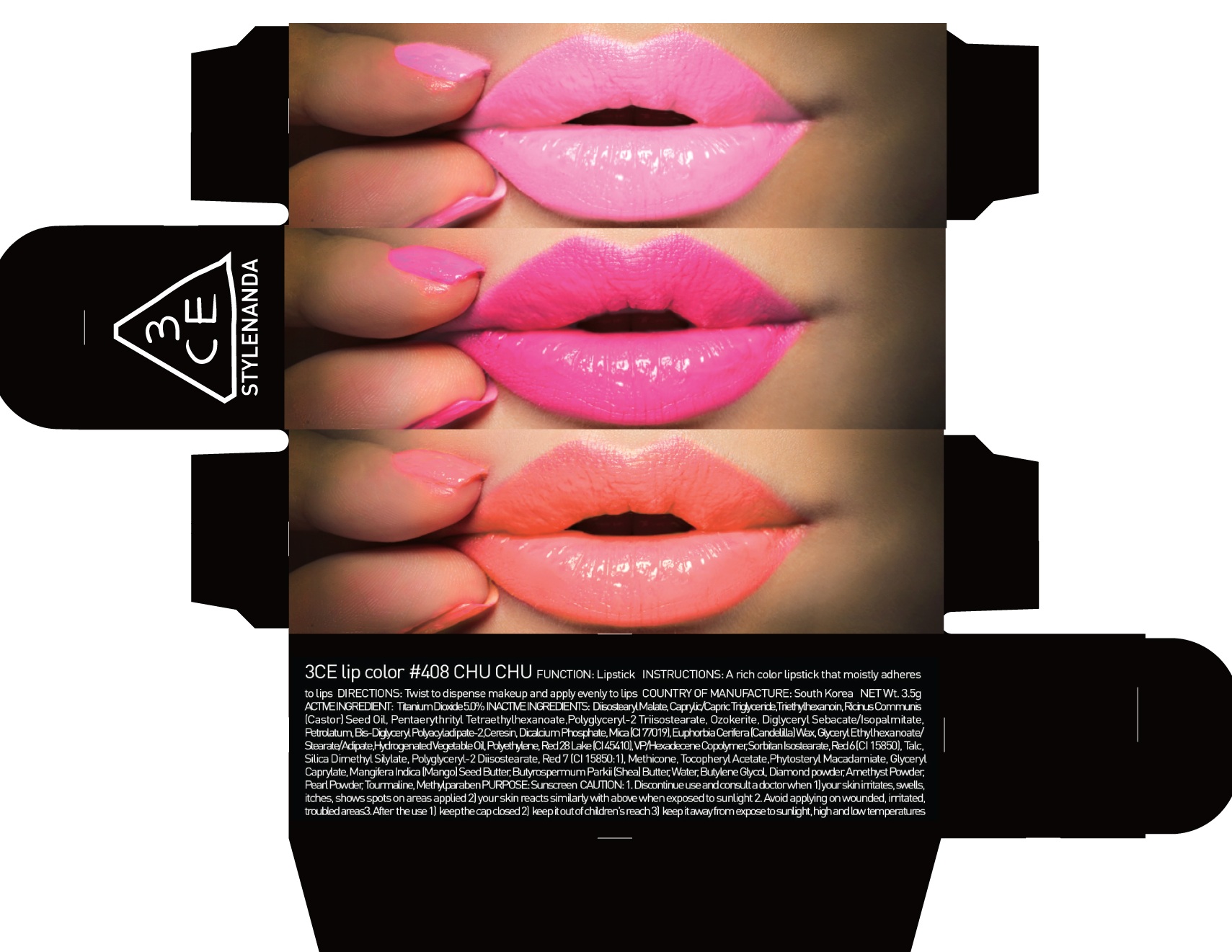 DRUG LABEL: 3CE LIP COLOR 408 CHU CHU
NDC: 60764-071 | Form: LIPSTICK
Manufacturer: Nanda Co., Ltd
Category: otc | Type: HUMAN OTC DRUG LABEL
Date: 20161007

ACTIVE INGREDIENTS: Titanium Dioxide 0.17 g/3.5 g
INACTIVE INGREDIENTS: Diisostearyl Malate; Triethylhexanoin

ACTIVE INGREDIENT

Active Ingredient: Titanium Dioxide 5.0%

INACTIVE INGREDIENT

Inactive Ingredients: Diisostearyl Malate, Caprylic/Capric Triglyceride, Triethylhexanoin, Ricinus Communis (Castor) Seed Oil, Pentaerythrityl Tetraethylhexanoate, Polyglyceryl-2 Triisostearate, Ozokerite, Diglyceryl Sebacate/Isopalmitate, Petrolatum, Bis-Diglyceryl Polyacyladipate-2, Ceresin, Dicalcium Phosphate, Mica (CI 77019), Euphorbia Cerifera (Candelilla) Wax, Glyceryl Ethylhexanoate/Stearate/Adipate, Hydrogenated Vegetable Oil, Polyethylene, Red 28 Lake (CI 45410), VP/Hexadecene Copolymer, Sorbitan Isostearate, Red 6 (CI 15850), Talc, Silica Dimethyl Silylate, Polyglyceryl-2 Diisostearate, Red 7 (CI 15850:1), Methicone, Tocopheryl Acetate, Phytosteryl Macadamiate, Glyceryl Caprylate, Mangifera Indica (Mango) Seed Butter, Butyrospermum Parkii (Shea) Butter, Water, Butylene Glycol, Diamond powder, Amethyst Powder, Pearl Powder, Tourmaline, Methylparaben

PURPOSE

Purpose: Sunscreen

CAUTION

CAUTION: 1. Discontinue use and consult a doctor when - your skin irritates, swells, itches, shows spots on areas applied - your skin reacts similarly with above when exposed to sunlight 2. Avoid applying on wounded, irritated, troubled areas 3. After the use - keep the cap closed - keep it out of children's reach - keep it away from expose to sunlight, high and low temperatures

DESCRIPTION

INSTRUCTIONS: A rich color lipstick that moistly adheres to lips.

Directions: Twist to dispense makeup and apply evenly to lips